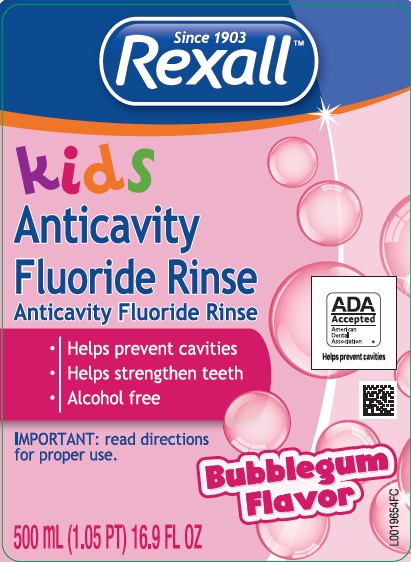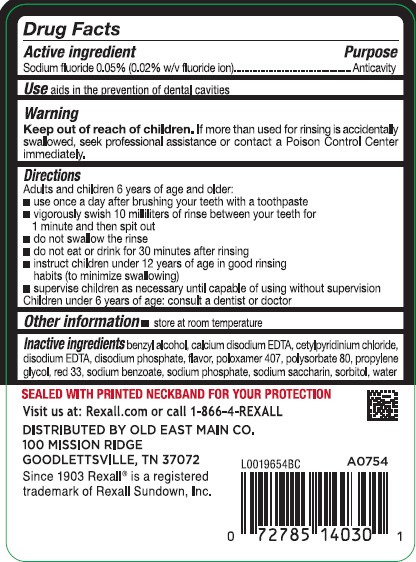 DRUG LABEL: Anticavity
NDC: 55910-030 | Form: RINSE
Manufacturer: Old East Main Co.
Category: otc | Type: HUMAN OTC DRUG LABEL
Date: 20260302

ACTIVE INGREDIENTS: SODIUM FLUORIDE 0.2 mg/1 mL
INACTIVE INGREDIENTS: BENZYL ALCOHOL; EDETATE CALCIUM DISODIUM ANHYDROUS; CETYLPYRIDINIUM CHLORIDE; EDETATE DISODIUM; SODIUM PHOSPHATE, DIBASIC, ANHYDROUS; POLOXAMER 407; POLYSORBATE 80; PROPYLENE GLYCOL; D&C RED NO. 33; SODIUM BENZOATE; SODIUM PHOSPHATE; SACCHARIN SODIUM; SORBITOL; WATER

Rexall 004.002/004AE
Anticavity Fluoride Rinse, Bubble Gum

Active ingredient

Sodium fluoride 0.05% (0.02% w/v fluoride ion)

Purpose

Anticavity

Use

aids in the prevention of dental cavities

Warnings

for this product

Keep out of reach of children.

If more than used for rinsing is accidentally swallowed, see professional assistance or contact a Poison Control Center immediately.

Directions

Adults and children 6 years of age and older:

- use once a day after brushing your teeth with a toothpaste
- vigorously swish 10 milliliters of rinse between your teeth for 1 minute and then spit out
- do not swallow the rinse
- do not eat or drink for 30 minutes after rinsing
- instruct children under 12 years of age in good rinsing habits (to minimize swallowing)
- supervise children as necessary until capable of using without supervision

Children under 6 years of age: consult a dentist or doctor

Other information

- store at room temperture

Inactive ingredients

benzyl alcohol, calcium disodium EDTA, cetylpyridinium chloride, disodium EDTA, disodium phosphate, flavor, poloxamer 407, polysorbate 80, propylene glycol, red 33, sodium benzoate, sodium phosphate, sodium saccharin, sorbitol, water

Tamper Evident Statement

Sealed with printed neckband for your protection

Adverse Reaction

Visit us at: Rexall.com or call 1-866-4-REXALL

DISTRIBUTED BY Old East Main CO,

100 MISSION RIDGE

GOODLETTSVILLE, TN 37072

Since 1903 Rexallis a registered trademark of Rexall Sundown, Inc.

Principal display panel

Since 1903

Rexall™

kids

Anticavity

Fluoride Rinse

Anticavitvy Fluoride Rinse

- Helps prevent cavities
- Helps strengthen teeth
- Alcohol free

IMPORTANT: read directions for proper use.

ADA Accepted

America Dental Association

Helps Prevent cavities

Bubblegum Flavor

500 mL (1.05 PT) 16.9 FL OZ